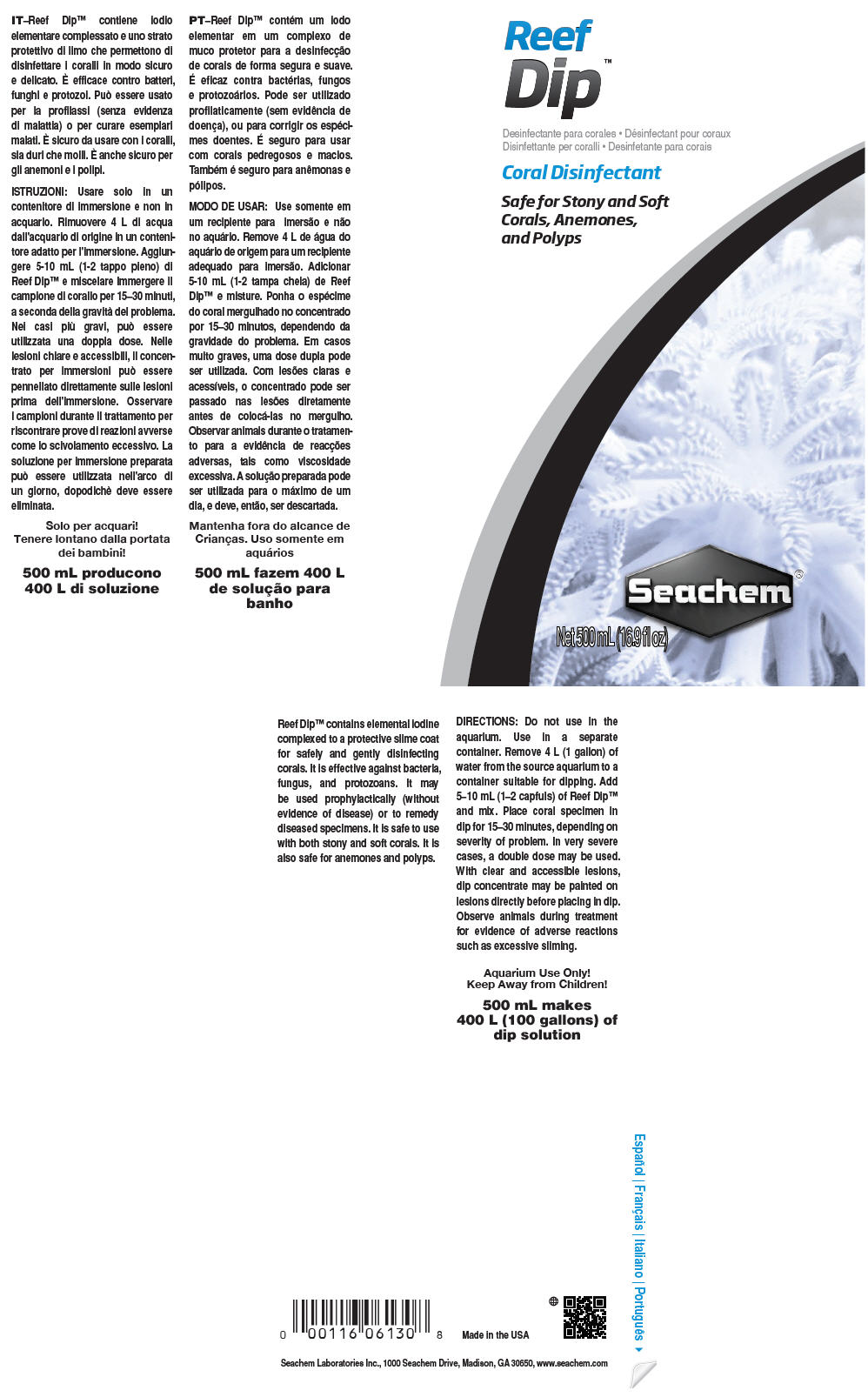 DRUG LABEL: Reef Dip
NDC: 55999-062 | Form: LIQUID
Manufacturer: Seachem Laboratories Inc.
Category: animal | Type: OTC ANIMAL DRUG LABEL
Date: 20180716

ACTIVE INGREDIENTS: Iodine 49.38 mg/1 mL

Reef Dip™

VETERINARY INDICATIONS

Reef Dip™ contains elemental iodine complexed to a protective slime coat for safely and gently disinfecting corals. It is effective against bacteria, fungus, and protozoans. It may be used prophylactically (without evidence of disease) or to remedy diseased specimens. It is safe to use with both stony and soft corals. It is also safe for anemones and polyps.

DOSAGE AND ADMINISTRATION

DIRECTIONS: Do not use in the aquarium. Use in a separate container. Remove 4 L (1 gallon) of water from the source aquarium to a container suitable for dipping. Add 5–10 mL (1–2 capfuls) of Reef Dip™ and mix. Place coral specimen in dip for 15–30 minutes, depending on severity of problem. In very severe cases, a double dose may be used. With clear and accessible lesions, dip concentrate may be painted on lesions directly before placing in dip. Observe animals during treatment for evidence of adverse reactions such as excessive sliming.

SAFE HANDLING WARNING

Aquarium Use Only!
Keep Away from Children!

500 mL makes 400 L (100 gallons) of dip solution

Made in the USA

Seachem Laboratories Inc., 1000 Seachem Drive, Madison, GA 30650, www.seachem.com

PRINCIPAL DISPLAY PANEL - 500 mL Bottle Label

Reef
Dip™

Coral Disinfectant

Safe for Stony and Soft
Corals, Anemones,
and Polyps

Seachem®

Net 500 mL (16.9 fl oz)